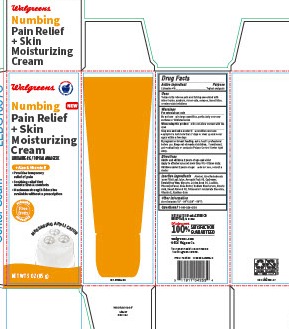 DRUG LABEL: Numbing Pain Relief
NDC: 0363-6261 | Form: CREAM
Manufacturer: Walgreen Company
Category: otc | Type: HUMAN OTC DRUG LABEL
Date: 20250328

ACTIVE INGREDIENTS: LIDOCAINE 4 g/100 g
INACTIVE INGREDIENTS: GLYCERIN; SODIUM BICARBONATE; STEARIC ACID; ALMOND OIL; TETRASODIUM GLUTAMATE DIACETATE; ALPHA-TOCOPHEROL; POLYSORBATE 60; CARBOMER 940; AVOCADO; LECITHIN, SUNFLOWER; CETOSTEARYL ALCOHOL; JOJOBA OIL; XANTHAN GUM; PHENOXYETHANOL; SHEA BUTTER; ALCOHOL; ALOE VERA LEAF

6261-Walgreen

Drug Facts

Active ingredient

Lidocaine 4%

Purpose

Topical analgesic

Uses

Temporarily relieves pain and itching associated with minor burns, sunburn, minor cuts, scrapes, insect bites, or minor skin irritations

WARNINGS

For external use only

DO NOT USE

- In large quantities, particularly over raw surfaces or blistered areas

WHEN USING

- Do not allow contact with the eyes

STOP USE

- condition worsens
- symptoms last more than 7 days or clear up and occur again within a few days

PREGNANCY OR BREAST FEEDING

If pregnant or breast feeding, ask a health professional before use.

Keep out of reach of children.

OVERDOSAGE

If swallowed, get medical help or contact a Poison Control Center right away.

Directions

Adults and children 2 years of age and older

- Apply to affected area not more than 3 to 4 times daily.

Children under 2 years of age

- do not use, consult a doctor

INACTIVE INGREDIENT

Alcohol, Aloe Barbadensis Inner Fillet Leaf Juice, Avocado Fruit Oil, Carbomer, Emulsifying Wax, Glycerin, Jojoba Seed Oil, Lecithin, Phenoxyethanol, Shea Butter, Sodium Bicarbonate, Stearic Acid, Sweet Almond Oil, Tetrasodium Glutamate Diacetate, Vitamin E, Xanthan Gum

Other information

store between 15° -30°C (59° -86°F)

QUESTIONS

1-800-925-4733

DISTRIBUTED BY: WALGREEN CO. DEERFIELD, IL 60015

Walgreens 100% SATISFACTION GUARANTEED

walgreens.com

©2024 Walgreen Co.

NDC 0363-6261-07

PACKAGE LABEL

Walgreens

Numbing Pain Relief + Skin Moisturizing Cream

LIDOCAINE 4% / TOPICAL ANALGESIC

+ Aloe & Vitamin E

Provides temporary relief of pain

Soothing relief that moisturizes & comforts

Maximum strength lidocaine available without a prescription

Free from Parabens, Fragrance

NET WT 3 OZ (85 g)